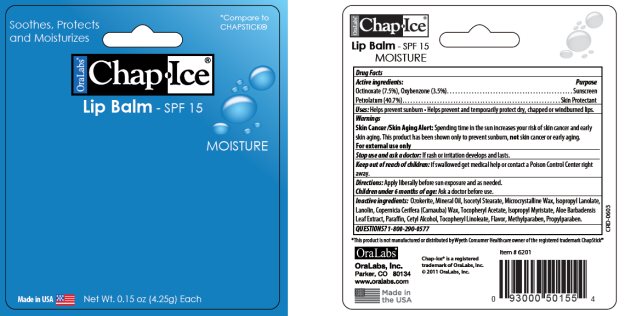 DRUG LABEL: ChapIce Moisture SPF 15 Lip Balm
NDC: 63645-140 | Form: STICK
Manufacturer: OraLabs
Category: otc | Type: HUMAN OTC DRUG LABEL
Date: 20250507

ACTIVE INGREDIENTS: OCTINOXATE 7.5 mg/1 g; OXYBENZONE 3.5 mg/1 g; PETROLATUM 40.7 mg/1 g
INACTIVE INGREDIENTS: CERESIN 17.13 mg/1 g; LIGHT MINERAL OIL 16.75 mg/1 g; ISOCETYL STEARATE 3.5 mg/1 g; MICROCRYSTALLINE WAX 3 mg/1 g; LANOLIN 1 mg/1 g; .ALPHA.-TOCOPHEROL ACETATE 0.6 mg/1 g

Drug Facts

Active ingredient

Octinoxate (7.5%), Oxybenzone (3.5%)

Petrolatum (40.7%)

Purpose

Sunscreen, Sunscreen, Skin Protectant

Keep Out of Reach of Children

If swallowed get medical help or contact a Poison Control Center right away.

Uses

Helps prevent sunburn. Helps prevent and temporarily protects dry, chapped or windburned lips.

Warnings

Skin Cancer/Skin Aging Alert: Spending time in the sun increases your risk of skin cancer and early skin aging. This product has been shown only to prevent sunburn, not skin cancer or early aging.

For external use only: Stop use and ask a doctor: if rash or irritation develops and lasts.

Directions

Apply liberally before sun exposure and as needed. Children under 6 months of age: Ask a doctor before use.

Inactive Ingredients

Ozokerite, Mineral Oil, Isocetyl Stearate, Microcrystalline Wax, Isopropyl Lanolate, Lanolin, Copernicia Cerifera (Carnauba) Wax, Tocopheryl Acetate, Isopropyl Myristate, Aloe Barbadenis Leaf Extract, Paraffin, Cetyl Alcohol, Tocerpheryl Linoleate, Flavor, Methylparaben, Propylparaben.